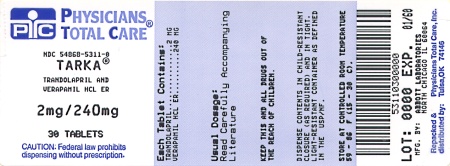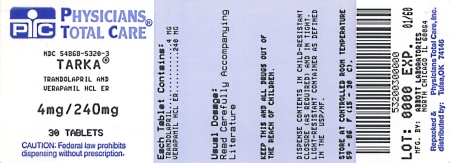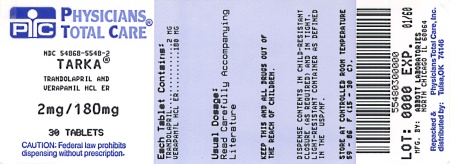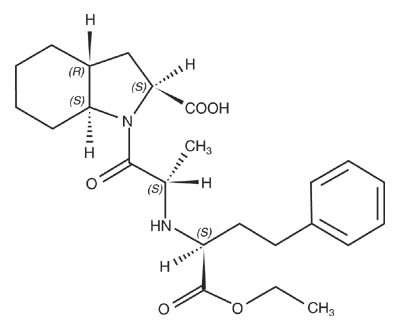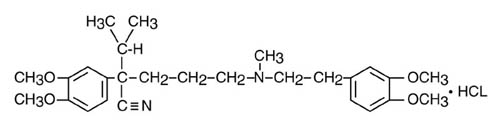 DRUG LABEL: Tarka
NDC: 54868-5548 | Form: TABLET, FILM COATED, EXTENDED RELEASE
Manufacturer: Physicians Total Care, Inc.
Category: prescription | Type: HUMAN PRESCRIPTION DRUG LABEL
Date: 20120213

ACTIVE INGREDIENTS: trandolapril 2 mg/1 1; verapamil hydrochloride 180 mg/1 1
INACTIVE INGREDIENTS: DOCUSATE SODIUM; ALCOHOL; hydroxypropyl cellulose; lactose; magnesium stearate; CELLULOSE, MICROCRYSTALLINE; POLYETHYLENE GLYCOL; povidone; water; silicon dioxide; sodium alginate; sodium stearyl fumarate; talc; titanium dioxide; starch, corn; HYPROMELLOSES

TARKA®
(trandolapril/verapamil hydrochloride ER tablets)

WARNING: FETAL TOXICITY

- When pregnancy is detected, discontinue TARKA as soon as possible.
- Drugs that act directly on the renin-angiotensin system can cause injury and death to the developing fetus (see WARNINGS: Fetal Toxicity).

DESCRIPTION

TARKA (trandolapril/verapamil hydrochloride ER) combines a slow release formulation of a calcium channel blocker, verapamil hydrochloride, and an immediate release formulation of an angiotensin converting enzyme inhibitor, trandolapril.

Verapamil Component

Verapamil hydrochloride is chemically described as benzeneacetonitrile, α[3-[[2-(3,4-dimethoxyphenyl)ethyl]methylamino]propyl]-3, 4-dimethoxy-α-(1-methylethyl) hydrochloride. Its empirical formula is C27H38N2O4 HCl and its structural formula is:

Verapamil hydrochloride is an almost white crystalline powder, with a molecular weight of 491.08. It is soluble in water, chloroform, and methanol. It is practically free of odor, with a bitter taste.

Trandolapril Component

Trandolapril is the ethyl ester prodrug of a nonsulfhydryl angiotensin converting enzyme (ACE) inhibitor, trandolaprilat. It is chemically described as (2S,3aR,7aS)-1-[(S)-N-[(S)-1-Carboxy-3-phenylpropyl]alanyl] hexahydro-2-indolinecarboxylic acid, 1-ethyl ester. Its empirical formula is C24 H34 N2O5 and its structural formula is:

Trandolapril is a white or almost white powder with a molecular weight of 430.54. It is soluble (>100 mg/mL) in chloroform, dichloromethane, and methanol.

TARKA tablets are formulated for oral administration, containing verapamil hydrochloride as a controlled release formulation and trandolapril as an immediate release formulation. The tablet strengths are trandolapril 2 mg/verapamil hydrochloride ER 180 mg, trandolapril 1 mg/verapamil hydrochloride ER 240 mg, trandolapril 2 mg/verapamil hydrochloride ER 240 mg, and trandolapril 4 mg/verapamil hydrochloride ER 240 mg. The tablets also contain the following ingredients: corn starch, dioctyl sodium sulfosuccinate, ethanol, hydroxypropyl cellulose, hypromellose, lactose monohydrate, magnesium stearate, microcrystalline cellulose, polyethylene glycol, povidone, purified water, silicon dioxide, sodium alginate, sodium stearyl fumarate, synthetic iron oxides, talc, and titanium dioxide.

CLINICAL PHARMACOLOGY

Verapamil hydrochloride and trandolapril have been used individually and in combination for the treatment of hypertension. For the four dosing strengths, the antihypertensive effect of the combination is approximately additive to the individual components.

Verapamil Component

Verapamil is a calcium channel blocker that exerts its pharmacologic effects by modulating the influx of ionic calcium across the cell membrane of the arterial smooth muscle as well as in conductile and contractile myocardial cells. Verapamil exerts antihypertensive effects by decreasing systemic vascular resistance, usually without orthostatic decreases in blood pressure or reflex tachycardia. During isometric or dynamic exercise, verapamil does not alter systolic cardiac function in patients with normal ventricular function. Verapamil does not alter total serum calcium levels.

Trandolapril Component

Trandolapril is de-esterified to its diacid metabolite, trandolaprilat. Both inhibit angiotensin-converting enzyme (ACE) in human subjects and in animals. Trandolaprilat is about 8 times more potent than trandolapril. ACE is a peptidyl dipeptidase that catalyzes the conversion of angiotensin I to the vasoconstrictor, angiotensin II. Angiotensin II also stimulates aldosterone secretion by the adrenal cortex.

Inhibition of ACE results in decreased plasma angiotensin II, which leads to decreased vasopressor activity and to decreased aldosterone secretion. The latter decrease may result in a small increase of serum potassium. In controlled clinical trials, treatment with TARKA resulted in mean increases in potassium of 0.1 mEq/L (see PRECAUTIONS). Removal of angiotensin II negative feedback on renin secretion leads to increased plasma renin activity (PRA).

ACE is identical to kininase II, an enzyme that degrades bradykinin. Whether increased levels of bradykinin, a potent vasodepressor peptide, play a role in the therapeutic effect of TARKA remains to be elucidated.

While the mechanism through which trandolapril lowers blood pressure is believed to be primarily suppression of the renin-angiotensin-aldosterone system, trandolapril has an antihypertensive effect even in patients with low renin hypertension. Trandolapril is an effective antihypertensive in all races studied. Both black patients (usually a predominantly low renin group) and non-black patients respond to 2 to 4 mg of trandolapril.

Pharmacokinetics and Metabolism

TARKA

Following a single oral dose of TARKA in healthy subjects, peak plasma concentrations are reached within 0.5-2 hours for trandolapril and within 4-15 hours for verapamil. Peak plasma concentrations of the active desmethyl metabolite of verapamil, norverapamil, are reached within 5-15 hours. Cleavage of the ester group converts trandolapril to its active diacid metabolite, trandolaprilat, which reaches peak plasma concentrations within 2-12 hours. The pharmacokinetics of trandolapril and trandolaprilat are not altered when trandolapril is administered in combination with verapamil, compared to monotherapy.

The AUC and Cmax for both verapamil and norverapamil are increased when 240 mg of controlled release verapamil is administered concomitantly with 4 mg trandolapril. The increase in Cmax is 54 and 30% and the AUC is increased by 65 and 32% for verapamil and norverapamil, respectively. Administration of TARKA 4/240 (4 mg trandolapril and 240 mg verapamil hydrochloride ER) with a high-fat meal does not alter the bioavailability of trandolapril whereas verapamil peak concentrations and area under the curve (AUC) decrease 37% and 28%, respectively. Food thus decreases verapamil bioavailability and the time to peak plasma concentration for both verapamil and norverapamil are delayed by approximately 7 hours. Both optical isomers of verapamil are similarly affected.

The elimination half life of trandolapril is about 6 hours. At steady state, the effective half-life of trandolaprilat is 22.5 hours. Like all ACE inhibitors, trandolaprilat also has a prolonged terminal elimination phase, involving a small fraction of administered drug, probably representing binding to plasma and tissue ACE.

The terminal half-life of verapamil is 6-11 hours. Steady-state plasma concentrations of the two components are achieved after about a week of once-daily dosing of TARKA. At steady-state, plasma concentrations of verapamil and trandolaprilat are up to two-fold higher than those observed after a single oral TARKA dose.

The pharmacokinetics of verapamil and trandolaprilat are significantly different in the elderly (≥65 years) than in younger subjects. The bioavailability of verapamil and norverapamil are increased by 87% and 77%, respectively, and that of trandolapril by approximately 35% in the elderly. AUCs are approximately 80% and 35% higher, respectively.

Verapamil Component

With the immediate release formulation, more than 90% of the orally administered dose is absorbed with peak plasma concentrations of verapamil observed 1 to 2 hours after dosing. A delayed rate but similar extent of absorption is observed for the sustained release formulation when compared to the immediate release formulation. Because of the rapid biotransformation of verapamil during its first pass through the portal circulation, absolute bioavailability ranges from 20% to 35%. A nonlinear correlation exists between verapamil dose and plasma concentrations.

In early dose titration with verapamil, a relationship exists between plasma concentrations of verapamil and prolongation of the PR interval. However, during chronic administration, this relationship may disappear. No relationship has been established between the plasma concentration of verapamil and reduction in blood pressure.

In healthy subjects, orally administered verapamil undergoes extensive metabolism in the liver. Twelve metabolites have been identified in plasma; all except norverapamil are present in trace amounts only. Approximately 70% of an administered dose is excreted as metabolites in the urine and 16% or more in the feces within 5 days. Urinary excretion of unchanged drug is about 3% to 4% of the dose. Verapamil is approximately 90% bound to plasma proteins.

In patients with hepatic insufficiency, verapamil clearance is decreased about 30% and the elimination half-life is prolonged up to 14 to 16 hours (see PRECAUTIONS). In patients with liver dysfunction, a dosage adjustment may be required. In the elderly (≥65 years), verapamil clearance is reduced resulting in increases in elimination half-life.

Trandolapril Component

Following oral administration of trandolapril, the absolute bioavailability of trandolapril is approximately 10% as trandolapril and 70% as trandolaprilat. Plasma concentrations of trandolaprilat but not trandolapril increase in proportion with dose. Plasma concentrations of trandolaprilat decline in a triphasic manner. The more prolonged terminal elimination phase probably represents a small fraction of dose saturably bound to ACE.

After an oral radiolabeled dose of trandolapril, excretion of trandolapril and metabolites account for 33% of the dose in the urine and about 66% in the feces. Less than 1% of the dose is excreted in the urine as unchanged drug. Serum protein binding of trandolapril is about 80%, and is independent of concentration. Binding of trandolaprilat is concentration-dependent, varying from 65% at 1000 ng/mL to 94% at 0.1 ng/mL, indicating saturation of binding with increasing concentration.

Compared to normal subjects, the plasma concentrations of trandolapril and trandolaprilat are approximately 2-fold greater and renal clearance is reduced by about 85% in patients with creatinine clearance below 30 mL/min and in patients on hemodialysis. Dosage adjustment is recommended in renally impaired patients (see DOSAGE AND ADMINISTRATION).

Following oral administration in patients with mild to moderate alcoholic cirrhosis, plasma concentrations of trandolapril and trandolaprilat were, respectively, 9-fold and 2-fold greater than in normal subjects, but inhibition of ACE activity was not affected. Lower doses should be considered in patients with hepatic insufficiency (see DOSAGE AND ADMINISTRATION).

Pharmacodynamics

TARKA

Verapamil does not interfere with ACE inhibition by trandolapril. Trandolapril does not alter the effect of verapamil on intra-cardiac conduction.

Verapamil Component

Verapamil dilates the main coronary arteries and coronary arterioles, both in normal and ischemic regions, and is a potent inhibitor of coronary artery spasm. This property increases myocardial oxygen delivery in patients with coronary artery spasm, and is responsible for the effectiveness of verapamil in vasospastic (Prinzmetal's or variant) as well as unstable angina at rest.

Verapamil regularly reduces the total systemic resistance (afterload) by dilating peripheral arterioles. By decreasing the influx of calcium, verapamil prolongs the effective refractory period within the AV node and slows AV conduction in a rate-related manner.

Normal sinus rhythm is usually not affected, but in patients with sick sinus syndrome, verapamil may interfere with sinus node impulse generation and may induce sinus arrest or sinoatrial block. Atrioventricular block can occur in patients without preexisting conduction defects (see WARNINGS).

Verapamil does not alter the normal atrial action potential or intraventricular conduction time, but depresses amplitude, velocity of depolarization and conduction in depressed atrial fibers. Verapamil may shorten the antegrade effective refractory period of accessory bypass tracts. Acceleration of ventricular rate and/or ventricular fibrillation has been reported in patients with atrial flutter or atrial fibrillation and a coexisting accessory AV pathway following administration of verapamil (see WARNINGS).

Hemodynamics and Myocardial Metabolism: Verapamil reduces afterload and myocardial contractility. Improved left ventricular diastolic function in patients with idiopathic hypertrophic subaortic stenosis (IHSS) and those with coronary heart disease has also been observed with verapamil therapy. In most patients, including those with organic cardiac disease, the negative inotropic action of verapamil is countered by a reduction of afterload and cardiac index is usually not reduced. However, in patients with severe left ventricular dysfunction (e.g., pulmonary wedge pressure about 20 mmHg or ejection fraction less than 30%), or in patients taking beta-adrenergic blocking agents or other cardio-depressant drugs, deterioration of ventricular function may occur (see DRUG INTERACTIONS).

Pulmonary Function: Verapamil does not induce bronchoconstriction and hence, does not impair ventilatory function.

Trandolapril Component

After a single 2 mg dose of trandolapril, inhibition of ACE activity reaches a maximum (70-85%) at 4 hours with about 10% decline at 24 hours. Eight days after dosing, ACE inhibition is still 40%.

Four placebo-controlled dose response studies were conducted using once daily oral dosing of trandolapril in doses from 0.25 to 16 mg per day in 827 black and non-black patients with mild to moderate hypertension. The minimal effective once daily dose was 1.0 mg in non-black patients and 2.0 mg in black patients. Further decreases in trough supine diastolic blood pressure were obtained in non-black patients with higher doses, and no further response was seen with doses above 4 mg (up to 16 mg). The antihypertensive effect diminished somewhat at the end of the dosing interval.

During chronic therapy, the maximum reduction in blood pressure with any dose is achieved within one week. Following 6 weeks of monotherapy in placebo-controlled trials in patients with mild to moderate hypertension, once daily doses of 2 to 4 mg lowered supine or standing systolic/diastolic blood pressure 24 hours after dosing by an average 7-10/4-5 mmHg below placebo responses in non-black patients. Once daily doses of 2 to 4 mg lowered blood pressures 4-6/3-4 mmHg below placebo responses in black patients.

CLINICAL STUDIES

In controlled clinical trials, once daily doses of TARKA, trandolapril 4 mg/verapamil HCl ER 240 mg or trandolapril 2 mg/verapamil HCl ER 180 mg, decreased placebo-corrected seated pressure (systolic/diastolic) 24 hours after dosing by about 7-12/6-8 mmHg. Each of the components of TARKA added to the antihypertensive effect. Treatment effects were consistent across age groups (<65, ≥65 years), and gender (male, female).

Blood pressure reductions were significantly greater for the TARKA 4/240 combination than for either of the components used alone.

The antihypertensive effects of TARKA have continued during therapy for at least 1 year.

INDICATIONS AND USAGE

TARKA is indicated for the treatment of hypertension.

This fixed combination drug is not indicated for the initial therapy of hypertension (see DOSAGE and ADMINISTRATION).

In using TARKA, consideration should be given to the fact that an angiotensin converting enzyme inhibitor, captopril, has caused agranulocytosis, particularly in patients with renal impairment or collagen vascular disease, and that available data are insufficient to show that trandolapril does not have similar risk (see WARNINGS -Neutropenia/Agranulocytosis).

CONTRAINDICATIONS

TARKA is contraindicated in patients who are hypersensitive to any ACE inhibitor or verapamil.

Because of the verapamil component, TARKA is contraindicated in:

1. Severe left ventricular dysfunction (see WARNINGS).
2. Hypotension (systolic pressure less than 90 mmHg) or cardiogenic shock.
3. Sick sinus syndrome (except in patients with a functioning artificial ventricular pacemaker).
4. Second- or third-degree AV block (except in patients with a functioning artificial ventricular pacemaker).
5. Patients with atrial flutter or atrial fibrillation and an accessory bypass tract (e.g. Wolff-Parkinson-White, Lown-Ganong-Levine syndromes) (see WARNINGS).

Because of the trandolapril component, TARKA is contraindicated in patients with a history of angioedema related to previous treatment with an angiotensin converting enzyme (ACE) inhibitor.

WARNINGS

Heart Failure

Verapamil Component

Verapamil has a negative inotropic effect which, in most patients, is compensated by its afterload reduction (decreased systemic vascular resistance) properties without a net impairment of ventricular performance. In clinical experience with 4,954 patients, 87 (1.8%) developed congestive heart failure or pulmonary edema. Verapamil should be avoided in patients with severe left ventricular dysfunction (e.g., ejection fraction less than 30%, pulmonary wedge pressure above 20 mmHg, or severe symptoms of cardiac failure) and in patients with any degree of ventricular dysfunction if they are receiving a beta adrenergic blocker (see DRUG INTERACTIONS). Patients with milder ventricular dysfunction should, if possible, be controlled with optimum doses of digitalis and/or diuretics before verapamil treatment (Note interactions with digoxin under: PRECAUTIONS).

Trandolapril Component

Trandolapril, as an ACE inhibitor, may cause excessive hypotension in patients with congestive heart failure (see WARNINGS - Hypotension).

Hypotension

Verapamil Component

Occasionally, the pharmacologic action of verapamil may produce a decrease in blood pressure below normal levels which may result in dizziness or symptomatic hypotension.

Trandolapril Component

Trandolapril can cause symptomatic hypotension. Like other ACE inhibitors, trandolapril has only rarely been associated with symptomatic hypotension in uncomplicated hypertensive patients. Symptomatic hypotension is most likely to occur in patients who are salt- or volume-depleted as a result of prolonged treatment with diuretics, dietary salt restriction, dialysis, diarrhea, or vomiting. Volume and/or salt depletion should be corrected before initiating treatment with trandolapril (see PRECAUTIONS -Drug Interactions and ADVERSE REACTIONS).

In controlled studies, hypotension was observed in 0.6% of patients receiving any combination of trandolapril and verapamil HCl ER.

In patients with concomitant congestive heart failure, with or without associated renal insufficiency, ACE inhibitor therapy may cause excessive hypotension, which may be associated with oliguria or azotemia, and, rarely, with acute renal failure and death (see DOSAGE AND ADMINISTRATION).

If symptomatic hypotension occurs, the patient should be placed in the supine position and, if necessary, normal saline may be administered intravenously. A transient hypotensive response is not a contraindication to further doses; however, lower doses of verapamil HCl ER and/or trandolapril or reduced concomitant diuretic therapy should be considered.

Elevated Liver Enzymes/Hepatic Failure

Verapamil Component

Elevations of transaminases with and without concomitant elevations in alkaline phosphatase and bilirubin have been reported. Such elevations have sometimes been transient and may disappear even in the face of continued verapamil treatment. Several cases of hepatocellular injury related to verapamil have been proven by rechallenge; half of these had clinical symptoms (malaise, fever, and/or right upper quadrant pain) in addition to elevations of SGOT, SGPT, and alkaline phosphatase.

Trandolapril Component

ACE inhibitors rarely have been associated with a syndrome of cholestatic jaundice, fulminant hepatic necrosis, and death. The mechanism of this syndrome is not understood. Patients receiving ACE inhibitors who develop jaundice should discontinue the ACE inhibitor and receive appropriate medical follow-up.

Liver abnormalities were noted in 3.2% of patients taking any of several combinations of trandolapril/verapamil doses. Periodic monitoring of liver function in patients taking TARKA is therefore prudent.

Accessory Bypass Tract (Wolff-Parkinson-White or Lown-Ganong-Levine Syndromes)

Verapamil Component

Some patients with paroxysmal and/or chronic atrial fibrillation or atrial flutter and a coexisting accessory AV pathway have developed increased antegrade conduction across the accessory pathway bypassing the AV node, producing a very rapid ventricular response or ventricular fibrillation after receiving intravenous verapamil (or digitalis). Although a risk of this occurring with oral verapamil has not been established, such patients receiving oral verapamil may be at risk and its use in these patients is contraindicated (see CONTRAINDICATIONS).

Treatment is usually DC-cardioversion. Cardioversion has been used safely and effectively after oral verapamil.

Atrioventricular Block

Verapamil Component

The effect of verapamil on AV conduction and the SA node may lead to asymptomatic first-degree AV block and transient bradycardia, sometimes accompanied by nodal escape rhythms. PR interval prolongation is correlated with verapamil plasma concentrations, especially during the early titration phases of therapy. Higher degrees of AV block, however, were infrequently (0.8%) observed. Marked first-degree block or progressive development to second- or third-degree AV block requires a reduction in dosage or, in rare instances, discontinuation of verapamil HCl and institution of appropriate therapy depending upon the clinical situation.

Patients with Hypertrophic Cardiomyopathy (IHSS)

Verapamil Component

In 120 patients with hypertrophic cardiomyopathy (most of them refractory or intolerant to propranolol) who received therapy with verapamil at doses up to 720 mg/day, a variety of serious adverse effects were seen. Three patients died in pulmonary edema; all had severe left ventricular outflow obstruction and a past history of left ventricular dysfunction. Eight other patients had pulmonary edema and/or severe hypotension; abnormally high (over 20 mmHg) capillary wedge pressure and a marked left ventricular outflow obstruction were present in most of these patients. Sinus bradycardia occurred in 11% of the patients, second-degree AV block in 4% and sinus arrest in 2%. It must be appreciated that this group of patients had a serious disease with a high mortality rate. Most adverse effects responded well to dose reduction and only rarely did verapamil have to be discontinued.

Anaphylactoid and Possibly Related Reactions

Presumably because angiotensin-converting enzyme inhibitors affect the metabolism of eicosanoids and polypeptides, including endogenous bradykinin, patients receiving ACE inhibitors, including trandolapril may be subject to a variety of adverse reactions, some of them serious.

Angioedema

Angioedema of the face, extremities, lips, tongue, glottis, and larynx has been reported in patients treated with ACE inhibitors including trandolapril. Symptoms suggestive of angioedema or facial edema occurred in 0.13% of trandolapril-treated patients. Two of the four cases were life-threatening and resolved without treatment or with medication (corticosteroids). Angioedema associated with laryngeal edema can be fatal. If laryngeal stridor or angioedema of the face, tongue or glottis occurs, treatment with TARKA should be discontinued immediately, the patient treated in accordance with accepted medical care and carefully observed until the swelling disappears. In instances where swelling is confined to the face and lips, the condition generally resolves without treatment; antihistamines may be useful in relieving symptoms. Where there is involvement of the tongue, glottis, or larynx, likely to cause airway obstruction, emergency therapy, including but not limited to subcutaneous epinephrine solution 1:1,000 (0.3 to 0.5 mL) should be promptly administered (see PRECAUTIONS and ADVERSE REACTIONS).

Anaphylactoid Reactions During Desensitization

Two patients undergoing desensitizing treatment with hymenoptera venom while receiving ACE inhibitors sustained life-threatening anaphylactoid reactions. In the same patients, these reactions did not occur when ACE inhibitors were temporarily withheld, but they reappeared when the ACE inhibitors were inadvertently readministered.

Anaphylactoid Reactions During Membrane Exposure

Anaphylactoid reactions have been reported in patients dialyzed with high-flux membranes and treated concomitantly with an ACE inhibitor. Anaphylactoid reactions have also been reported in patients undergoing low-density lipoprotein apheresis with dextran sulfate absorption.

Neutropenia/Agranulocytosis

Trandolapril Component

Another ACE inhibitor, captopril, has been shown to cause agranulocytosis and bone marrow depression rarely in patients with uncomplicated hypertension, but more frequently in patients with renal impairment, especially if they also have a collagen-vascular disease such as systemic lupus erythematosus or scleroderma. Available data from clinical trials of trandolapril or TARKA are insufficient to show that trandolapril does not cause agranulocytosis at similar rates. As with other ACE inhibitors, periodic monitoring of white blood cell counts in patients with collagen-vascular disease and/or renal disease should be considered.

Fetal Toxicity

Pregnancy Category D

Trandolapril Component

Use of drugs that act on the renin-angiotensin system during the second and third trimesters of pregnancy reduces fetal renal function and increases fetal and neonatal morbidity and death. Resulting oligohydramnios can be associated with fetal lung hypoplasia and skeletal deformations. Potential neonatal adverse effects include skull hypoplasia, anuria, hypotension, renal failure, and death. When pregnancy is detected, discontinue TARKA as soon as possible. These adverse outcomes are usually associated with use of these drugs in the second and third trimester of pregnancy. Most epidemiologic studies examining fetal abnormalities after exposure to antihypertensive use in the first trimester have not distinguished drugs affecting the renin-angiotensin system from other antihypertensive agents. Appropriate management of maternal hypertension during pregnancy is important to optimize outcomes for both mother and fetus.

In the unusual case that there is no appropriate alternative to therapy with drugs affecting the renin-angiotensin system for a particular patient, apprise the mother of the potential risk to the fetus. Perform serial ultrasound examinations to assess the intra-amniotic environment. If oligohydramnios is observed, discontinue TARKA, unless it is considered lifesaving for the mother. Fetal testing may be appropriate, based on the week of pregnancy. Patients and physicians should be aware, however, that oligohydramnios may not appear until after the fetus has sustained irreversible injury. Closely observe infants with histories of in utero exposure to TARKA for hypotension, oliguria, and hyperkalemia (see PRECAUTIONS, Pediatric Use).

Doses of 0.8 mg/kg/day (9.4 mg/m2/day) in rabbits, 1000 mg/kg/day (7000 mg/m2/day) in rats, and 25 mg/kg/day (295 mg/m2/day) in cynomolgus monkeys did not produce teratogenic effects. These doses represent 10 and 3 times (rabbits), 1250 and 2564 times (rats), and 312 and 108 times (monkeys) the maximum projected human dose of 4 mg based on body-weight and body-surface-area, respectively assuming a 50 kg woman.

Trandolapril in doses of 0.8 mg/kg/day in rabbits, 100.0 mg/kg/day in rats, and 25 mg/kg/day in cynomolgus monkeys (10, 1250, and 312 times the maximum projected human dose, respectively, assuming a 50 kg woman) did not produce teratogenic effects.

PRECAUTIONS

Use in Patients with Impaired Hepatic Function

TARKA has not been evaluated in subjects with impaired hepatic function.

Verapamil Component

Since verapamil is highly metabolized by the liver, it should be administered cautiously to patients with impaired hepatic function. Severe liver dysfunction prolongs the elimination half-life of immediate release verapamil to about 14 to 16 hours; hence, approximately 30% of the dose given to patients with normal liver function should be administered to these patients.

Careful monitoring for abnormal prolongation of the PR interval or other signs of excessive pharmacologic effects (see OVERDOSAGE) should be carried out.

Trandolapril Component

Trandolapril and trandolaprilat concentrations increase in patients with impaired liver function.

Use in Patients with Impaired Renal Function

TARKA has not been evaluated in patients with impaired renal function.

Verapamil Component

About 70% of an administered dose of verapamil is excreted as metabolites in the urine. Verapamil is not removed by hemodialysis. Until further data are available, verapamil should be administered cautiously to patients with impaired renal function. These patients should be carefully monitored for abnormal prolongation of the PR interval or other signs of overdosage (see OVERDOSAGE).

Trandolapril Component

As a consequence of inhibiting the renin-angiotensin-aldosterone system, changes in renal function may be anticipated in susceptible individuals. In patients with severe heart failure whose renal function may depend on the activity of the renin-angiotensin-aldosterone system, treatment with ACE inhibitors, including trandolapril, may be associated with oliguria and/or progressive azotemia and rarely with acute renal failure and/or death.

In hypertensive patients with unilateral or bilateral renal artery stenosis, increases in blood urea nitrogen and serum creatinine have been observed in some patients following ACE inhibitor therapy. These increases were almost always reversible upon discontinuation of the ACE inhibitor and/or diuretic therapy. In such patients, renal function should be monitored during the first few weeks of therapy.

Some hypertensive patients with no apparent pre-existing renal vascular disease have developed increases in blood urea and serum creatinine, usually minor and transient, especially when ACE inhibitors have been given concomitantly with a diuretic. This is more likely to occur in patients with pre-existing renal impairment. Dosage reduction and/or discontinuation of any diuretic and/or the ACE inhibitor may be required.

Evaluation of hypertensive patients should always include assessment of renal function (see DOSAGE AND ADMINISTRATION).

Use in Patients with Attenuated (Decreased) Neuromuscular Transmission

Verapamil Component

It has been reported that verapamil decreases neuromuscular transmission in patients with Duchenne's muscular dystrophy, and that verapamil prolongs recovery from the neuromuscular blocking agent vecuronium. It may be necessary to decrease the dosage of verapamil when it is administered to patients with attenuated neuromuscular transmission (see PRECAUTIONS - Surgery/Anesthesia).

Hyperkalemia and Potassium-sparing Diuretics

Trandolapril Component

In clinical trials, hyperkalemia (serum potassium > 6.00 mEq/L) occurred in approximately 0.4 percent of hypertensive patients receiving trandolapril and in 0.8% of patients receiving a dose of trandolapril (0.5-8 mg) in combination with a dose of verapamil SR (120-240 mg). In most cases, elevated serum potassium levels were isolated values, which resolved despite continued therapy. None of these patients were discontinued from the trials because of hyperkalemia. Risk factors for the development of hyperkalemia include renal insufficiency, diabetes mellitus, and the concomitant use of potassium-sparing diuretics, potassium supplements, and/or potassium-containing salt substitutes, which should be used cautiously, if at all, with trandolapril (see PRECAUTIONS - Drug Interactions).

Cough

Presumably due to the inhibition of the degradation of endogenous bradykinin, persistent nonproductive cough has been reported with all ACE inhibitors, always resolving after discontinuation of therapy. ACE inhibitor-induced cough should be considered in the differential diagnosis of cough. In controlled trials of trandolapril, cough was present in 2% of trandolapril patients and 0% of patients given placebo. There was no evidence of a relationship to dose.

Surgery/anesthesia

Trandolapril Component

In patients undergoing major surgery or during anesthesia with agents that produce hypotension, trandolapril will block angiotensin II formation secondary to compensatory renin release. If hypotension occurs and is considered to be due to this mechanism, it can be corrected by volume expansion (see PRECAUTIONS - Use in Patients with Attenuated (Decreased) Neuromuscular Transmission).

Drug Interactions

In vitro metabolic studies indicate that verapamil is metabolized by cytochrome P450 including CYP3A4, CYP1A2, CYP2C8, CYP2C9 and CYP2C18. Verapamil has been shown to be an inhibitor of CYP3A4 enzymes and P-glycoprotein (P-gp).

Clinically significant interactions have been reported with inhibitors of CYP3A4 (e.g. erythromycin, ritonavir) causing elevation of plasma levels of verapamil while inducers of CYP3A4 (e.g. rifampin) have caused a lowering of plasma levels of verapamil. Therefore, patients receiving inhibitors or inducers of the cytochrome P450 system should be monitored for drug interactions.

Digitalis

Clinical use of verapamil in digitalized patients has shown the combination to be well tolerated if digoxin doses are properly adjusted. Chronic verapamil treatment can increase serum digoxin levels by 50 to 75% during the first week of therapy, and this can result in digoxin toxicity. In patients with hepatic cirrhosis, the influence of verapamil on digoxin kinetics is magnified. Verapamil may reduce total body clearance and extrarenal clearance of digitoxin by 27% and 29%, respectively. Maintenance digoxin doses should be reduced when verapamil is administered, and the patient should be carefully monitored to avoid over- or under-digitalization. Whenever overdigitalization is suspected, the daily dose of digoxin should be reduced or temporarily discontinued. Upon discontinuation of any verapamil-containing regime including TARKA (trandolapril/verapamil hydrochloride ER), the patient should be reassessed to avoid underdigitalization. No clinically significant pharmacokinetic interaction has been found between trandolapril (or its metabolites) and digoxin.

Lithium

Verapamil Component

Increased sensitivity to the effects of lithium (neurotoxicity) has been reported during concomitant verapamil-lithium therapy with either no change or an increase in serum lithium levels. Increased serum lithium levels and symptoms of lithium toxicity have been reported in patients receiving concomitant lithium and ACE inhibitor therapy. TARKA and lithium should be coadministered with caution, and frequent monitoring of serum lithium levels is recommended. If a diuretic is also used, the risk of lithium toxicity may be increased.

Clarithromycin

Hypotension, bradyarrhythmias, and lactic acidosis have been observed in patients receiving concurrent clarithromycin.

Erythromycin

Hypotension, bradyarrhythmias, and lactic acidosis have been observed in patients receiving concurrent erythromycin ethylsuccinate.

Cimetidine

The interaction between cimetidine and chronically administered verapamil has not been studied. Variable results on clearance have been obtained in acute studies of healthy volunteers; clearance of verapamil was either reduced or unchanged. No clinically significant pharmacokinetic interaction has been found between trandolapril (or its metabolites) and cimetidine.

Antiarrhythmic Agents

Verapamil Component

Disopyramide Phosphate

Data on possible interactions between verapamil and disopyramide phosphate are not available. Therefore, disopyramide should not be administered within 48 hours before or 24 hours after verapamil administration.

Flecainide

A study of healthy volunteers showed that the concomitant administration of flecainide and verapamil may have additive effects on myocardial contractility, AV conduction, and repolarization. Concomitant therapy with flecainide and verapamil may result in additive negative inotropic effect and prolongation of atrioventricular conduction.

Quinidine

In a small number of patients with hypertrophic cardiomyopathy (IHSS), concomitant use of verapamil and quinidine resulted in significant hypotension. Until further data are obtained, combined therapy of verapamil and quinidine in patients with hypertrophic cardiomyopathy should probably be avoided.

The electrophysiological effects of quinidine and verapamil on AV conduction were studied in 8 patients. Verapamil significantly counteracted the effects of quinidine on AV conduction. There has been a report of increased quinidine levels during verapamil therapy.

Antihypertensive Agents

Concomitant use of TARKA with other antihypertensive agents including diuretics, vasodilators, beta-adrenergic blockers, and alpha-antagonists may result in additive hypotensive effects. There are reports that verapamil may result in higher concentrations of the alpha-agonists prazosin and terazosin.

Beta Blockers

Verapamil Component

Concomitant therapy with beta-adrenergic blockers and verapamil may result in additive negative effects on heart rate, atrioventricular conduction, and/or cardiac contractility. Drug interaction studies have indicated that the maximum concentrations of metoprolol and propanolol are increased after the administration of verapamil. The use of verapamil in combination with a beta-adrenergic blocker should be used only with caution, and close monitoring.

Asymptomatic bradycardia (36 beats/min) with a wandering atrial pacemaker has been observed in a patient receiving concomitant timolol (a beta-adrenergic blocker) eyedrops and oral verapamil.

Concomitant Diuretic Therapy

Trandolapril Component

As with other ACE inhibitors, patients on diuretics, especially those on recently instituted diuretic therapy, may occasionally experience an excessive reduction of blood pressure after initiation of therapy with TARKA. The possibility of exacerbation of hypotensive effects with TARKA may be minimized by either discontinuing the diuretic or cautiously increasing salt intake prior to initiation of treatment with TARKA. If it is not possible to discontinue the diuretic, the starting dose of TARKA should be reduced (see DOSAGE AND ADMINISTRATION). No clinically significant pharmacokinetic interaction has been found between trandolapril (or its metabolites) and furosemide.

Agents Increasing Serum Potassium

Trandolapril Component

Trandolapril can attenuate potassium loss caused by thiazide diuretics and increase serum potassium when used alone. Use of potassium-sparing diuretics (spironolactone, triamterene, or amiloride), potassium supplements, or potassium-containing salt substitutes concomitantly with ACE inhibitors can increase the risk of hyperkalemia. If concomitant use of such agents is indicated, they should be used with caution and with appropriate monitoring of serum potassium (see PRECAUTIONS).

HMG-CoA Reductase Inhibitors (“Statins”)

Verapamil component

The use of HMG-CoA reductase inhibitors that are CYP3A4 substrates in combination with verapamil has been associated with reports of myopathy/rhabdomyolysis.

Co-administration of multiple doses of 10 mg of verapamil with 80 mg simvastatin resulted in exposure to simvastatin 2.5-fold that following simvastatin alone. Limit the dose of simvastatin in patients on verapamil to 10 mg daily. Limit the daily dose of lovastatin to 40 mg. Lower starting and maintenance doses of other CYP3A4 substrates (e.g., atorvastatin) may be required as verapamil may increase the plasma concentration of these drugs.

Non-Steroidal Anti-Inflammatory Agents including Selective Cyclooxygenase-2 Inhibitors (COX-2 Inhibitors)

Trandolapril component

In patients who are elderly, volume-depleted (including those on diuretic therapy), or with compromised renal function, co-administration of NSAIDs, including selective COX-2 inhibitors, with ACE inhibitors, including trandolapril, may result in deterioration of renal function, including possible acute renal failure. These effects are usually reversible. Monitor renal function periodically in patients receiving trandolapril and NSAID therapy.

The antihypertensive effect of ACE inhibitors, including trandolapril may be attenuated by NSAIDs.

Other (Verapamil Component)

Nitrates

Verapamil has been given concomitantly with short- and long-acting nitrates without any undesirable drug interactions. The pharmacologic profile of both drugs and the clinical experience suggest beneficial interactions.

Carbamazepine

Verapamil may increase carbamazepine concentrations during combined therapy. This may produce carbamazepine side effects such as diplopia, headache, ataxia, or dizziness.

Anti-infective Agents

Therapy with rifampin may markedly reduce oral verapamil bioavailability. There have been reports that erythromycin and telithromycin may increase concentrations of verapamil.

Barbiturates

Phenobarbital therapy may increase verapamil clearance.

Immunosuppressive Agents

Verapamil therapy may increase serum levels of cyclosporin, sirolimus and tacrolimus.

Theophylline

Verapamil therapy may inhibit the clearance and increase the plasma levels of theophylline.

Tranquilizers/ Anti-depressants

Due to metabolism via the CYP enzyme system, there have been reports that verapamil may increase the concentrations of buspirone, midazolam, almotriptan and imipramine.

Colchicine

Colchicine is a substrate for both CYP3A and the efflux transporter, P-gp. Verapamil is known to inhibit CYP3A and P-gp. When verapamil and colchicine are administered together, the potential inhibition of P-gp and/or CYP3A by verapamil may lead to increased exposure to colchicine (see PRECAUTIONS-Drug Interactions).

Other

Concentrations of verapamil may be increased by the concomitant administration of protease inhibitors such as ritonavir, and reduced by the concomitant administration of sulfinpyrazone, or St John’s Wort.

Concentrations of doxorubicin may be increased by the administration of verapamil.

There have been reports that verapamil may elevate the concentrations of the oral anti-diabetic glyburide.

Inhalation Anesthetics

Animal experiments have shown that inhalation anesthetics depress cardiovascular activity by decreasing the inward movement of calcium ions. When used concomitantly, inhalation anesthetics and calcium antagonists, such as verapamil, should be titrated carefully to avoid excessive cardiovascular depression.

Neuromuscular Blocking Agents

Clinical data and animal studies suggest that verapamil may potentiate the activity of neuromuscular blocking agents (curare-like and depolarizing). It may be necessary to decrease the dose of verapamil and/or the dose of the neuromuscular blocking agent when the drugs are used concomitantly.

Gold

Nitritoid reactions (symptoms include facial flushing, nausea, vomiting and hypotension) have been reported rarely in patients on therapy with injectable gold (sodium aurothiomalate) and concomitant ACE inhibitor therapy including TARKA.

Other (Trandolapril Component)

No clinically significant pharmacokinetic interaction has been found between trandolapril (or its metabolites) and nifedipine.

The anticoagulant effect of warfarin was not significantly changed by trandolapril.

Anti-diabetic Agents

The concomitant use of ACE inhibitors such as trandolapril with antidiabetic medications (insulin or oral hypoglycemic agents) may result in increased blood glucose lowering effects.

Carcinogenesis, Mutagenesis, Impairment of Fertility

Verapamil Component

An 18-month toxicity study in rats, at a low multiple (6 fold) of the maximum recommended human dose, and not the maximum tolerated dose, did not suggest a tumorigenic potential. There was no evidence of a carcinogenic potential of verapamil administered in the diet of rats for two years at doses of 10, 35, and 120 mg/kg per day or approximately 1x, 3.5x, and 12x, respectively, the maximum recommended human daily dose (480 mg per day or 9.6 mg/kg/day).

Verapamil was not mutagenic in the Ames test in 5 test strains at 3 mg per plate, with or without metabolic activation.

Studies in female rats at daily dietary doses up to 5.5 times (55 mg/kg/day) the maximum recommended human dose did not show impaired fertility. Effects on male fertility have not been determined.

Long-term studies were conducted with oral trandolapril administered by gavage to mice (78 weeks) and rats (104 and 106 weeks). No evidence of carcinogenic potential was seen in mice dosed up to 25 mg/kg/day (85 mg/m^2/day) or rats dosed up to 8 mg/kg/day (60 mg/m^2/day). These doses are 313 and 32 times (mice), and 100 and 23 times (rats) the maximum recommended human daily dose (MRHDD) of 4 mg based on body-weight and body-surface-area, respectively assuming a 50 kg individual. The genotoxic potential of trandolapril was evaluated in the microbial mutagenicity (Ames) test, the point mutation and chromosome aberration assays in Chinese hamster V79 cells, and the micronucleus test in mice. There was no evidence of mutagenic or clastogenic potential in these in vitro and in vivo assays.

Reproduction studies in rats did not show any impairment of fertility at doses up to 100 mg/kg/day (710 mg/m^2/day) of trandolapril, or 1250 and 260 times the MRHDD on the basis of body-weight and body-surface-area, respectively.

Pregnancy

Female patients of childbearing age should be told about the consequences of exposure to TARKA during pregnancy. Discuss treatment options with women planning to become pregnant. Patients should be asked to report pregnancies to their physicians as soon as possible.

Nursing Mothers

Verapamil is excreted in human milk. Radiolabeled trandolapril or its metabolites are secreted in rat milk. TARKA should not be administered to nursing mothers.

Geriatric Use

In placebo-controlled studies, where 23% of patients receiving TARKA were 65 years and older, and 2.4% were 75 years and older, no overall differences in effectiveness or safety were observed between these patients and younger patients. However, greater sensitivity of some older individual patients cannot be ruled out.

Pediatric Use

Neonates with a history of in utero exposure to TARKA:

If oliguria or hypotension occurs, direct attention toward support of blood pressure and renal perfusion. Exchange transfusions or dialysis may be required as a means of reversing hypotension and/or substituting for disordered renal function.

The safety and effectiveness of TARKA in children below the age of 18 have not been established.

Animal Pharmacology and/or Animal Toxicology

In chronic animal toxicology studies, verapamil caused lenticular and/or suture line changes at 30 mg/kg/day or greater and frank cataracts at 62.5 mg/kg/day or greater in the beagle dog but not the rat. Development of cataracts due to verapamil has not been reported in man.

ADVERSE REACTIONS

TARKA has been evaluated in over 1,957 subjects and patients. Of these, 541 patients, including 23% elderly patients, participated in U.S. controlled clinical trials, and 251 were studied in foreign controlled clinical trials. In clinical trials with TARKA, no adverse experiences peculiar to this combination drug have been observed. Adverse experiences that have occurred have been limited to those that have been previously reported with verapamil or trandolapril. TARKA has been evaluated for long-term safety in 272 patients treated for 1 year or more. Adverse experiences were usually mild and transient.

Discontinuation of therapy because of adverse events in U.S. placebo-controlled hypertension studies was required in 2.6% and 1.9% of patients treated with TARKA and placebo, respectively.

Adverse experiences occurring in 1% or more of the 541 patients in placebo-controlled hypertension trials who were treated with a range of trandolapril (0.5-8 mg) and verapamil (120-240 mg) combinations are shown below.

ADVERSE EVENTS OCCURRING in ≥ 1% of TARKA PATIENTS IN U.S. PLACEBO-CONTROLLED TRIALS
 | TARKA (N = 541) % Incidence (% Discontinuance) | PLACEBO (N = 206) % Incidence (% Discontinuance)
AV Block First Degree | 3.9 (0.2) | 0.5 (0.0)
Bradycardia | 1.8 (0.0) | 0.0 (0.0)
Bronchitis | 1.5 (0.0) | 0.5 (0.0)
Chest Pain | 2.2 (0.0) | 1.0 (0.0)
Constipation | 3.3 (0.0) | 1.0 (0.0)
Cough | 4.6 (0.0) | 2.4 (0.0)
Diarrhea | 1.5 (0.2) | 1.0 (0.0)
Dizziness | 3.1 (0.0) | 1.9 (0.5)
Dyspnea | 1.3 (0.4) | 0.0 (0.0)
Edema | 1.3 (0.0) | 2.4 (0.0)
Fatigue | 2.8 (0.4) | 2.4 (0.0)
Headache(s)^+ | 8.9 (0.0) | 9.7 (0.5)
Increased Liver Enzymes* | 2.8 (0.2) | 1.0 (0.0)
Nausea | 1.5 (0.2) | 0.5 (0.0)
Pain Extremity(ies) | 1.1 (0.2) | 0.5 (0.0)
Pain Back^+ | 2.2 (0.0) | 2.4 (0.0)
Pain Joint(s) | 1.7 (0.0) | 1.0 (0.0)
Upper Respiratory Tract Infection(s)^+ | 5.4 (0.0) | 7.8 (0.0)
Upper Respiratory Tract Congestion^+ | 2.4 (0.0) | 3.4 (0.0)
* Also includes increase in SGPT, SGOT, Alkaline Phosphatase
+ Incidence of adverse events is higher in Placebo group than TARKA patients

Other clinical adverse experiences possibly, probably, or definitely related to drug treatment occurring in 0.3% or more of patients treated with trandolapril/verapamil combinations with or without concomitant diuretic in controlled or uncontrolled trials (N = 990) and less frequent, clinically significant events (in italics) include the following:

Cardiovascular

Angina, AV block second degree, bundle branch block, edema, flushing, hypotension, myocardial infarction , palpitations, premature ventricular contractions, nonspecific ST-T changes, near syncope, tachycardia.

Central Nervous System

Drowsiness, hypesthesia, insomnia, loss of balance, paresthesia, vertigo.

Dermatologic

Pruritus, rash.

Emotional, Mental, Sexual States

Anxiety, impotence, abnormal mentation.

Eye, Ear, Nose, Throat

Epistaxis, tinnitus, upper respiratory tract infection, blurred vision.

Gastrointestinal

Diarrhea, dyspepsia, dry mouth, nausea.

General Body Function

Chest pain, malaise, weakness.

Genitourinary

Endometriosis, hematuria, nocturia, polyuria, proteinuria.

Hemopoietic

Decreased leukocytes, decreased neutrophils.

Musculoskeletal System

Arthralgias/myalgias, gout (increased uric acid).

Pulmonary

Dyspnea.

Angioedema

Angioedema has been reported in 3 (0.15%) patients receiving TARKA in U.S. and foreign studies (N = 1,957). Angioedema associated with laryngeal edema may be fatal. If angioedema of the face, extremities, lips, tongue, glottis, and/or larynx occurs, treatment with TARKA should be discontinued and appropriate therapy instituted immediately (see WARNINGS).

Hypotension

(See WARNINGS.) In hypertensive patients, hypotension occurred in 0.6% and near syncope occurred in 0.1%. Hypotension or syncope was a cause for discontinuation of therapy in 0.4% of hypertensive patients.

Treatment of Acute Cardiovascular Adverse Reactions

The frequency of cardiovascular adverse reactions which require therapy is rare, hence, experience with their treatment is limited. Whenever severe hypotension or complete AV block occur following oral administration of TARKA (verapamil component), the appropriate emergency measures should be applied immediately, e.g., intravenously administered isoproterenol HCl, levarterenol bitartrate, atropine (all in the usual doses), or calcium gluconate (10% solution). In patients with hypertrophic cardiomyopathy (IHSS), alpha-adrenergic agents (phenylephrine, metaraminol bitartrate or methoxamine) should be used to maintain blood pressure, and isoproterenol and levarterenol should be avoided. If further support is necessary, inotropic agents (dopamine or dobutamine) may be administered. Actual treatment and dosage should depend on the severity and the clinical situation and the judgment and experience of the treating physician.

Other adverse experiences (in addition to those in table and listed above) that have been reported with the individual components are listed below.

Verapamil Component

Cardiovascular

(See WARNINGS.) CHF/pulmonary edema, AV block 3°, atrioventricular dissociation, claudication, purpura (vasculitis), syncope.

Digestive System

Gingival hyperplasia. Reversible, (upon discontinuation of verapamil) nonobstructive, paralytic ileus has been infrequently reported in association with the use of verapamil.

Hemic and Lymphatic

Ecchymosis or bruising.

Nervous System

Cerebrovascular accident, confusion, psychotic symptoms, shakiness, somnolence.

Skin

Exanthema, hair loss, hyperkeratosis, maculae, sweating, urticaria, Stevens-Johnson syndrome, erythema multiform.

Urogenital

Gynecomastia, galactorrhea/hyperprolactinemia, increased urination, spotty menstruation.

Trandolapril Component

Emotional, Mental, Sexual States

Decreased libido.

Gastrointestinal

Pancreatitis.

Clinical Laboratory Test Findings

Hematology

(See WARNINGS). Low white blood cells, low neutrophils, low lymphocytes, low platelets.

Serum Electrolytes

Hyperkalemia (see PRECAUTIONS), hyponatremia.

Renal Function Tests

Increases in creatinine and blood urea nitrogen levels occurred in 1.1 percent and 0.3 percent, respectively, of patients receiving TARKA with or without hydrochlorothiazide therapy. None of these increases required discontinuation of treatment. Increases in these laboratory values are more likely to occur in patients with renal insufficiency or those pretreated with a diuretic and, based on experience with other ACE inhibitors, would be expected to be especially likely in patients with renal artery stenosis (see PRECAUTIONS and WARNINGS).

Liver Function Tests

Elevations of liver enzymes (SGOT, SGPT, LDH, and alkaline phosphatase) and/or serum bilirubin occurred. Discontinuation for elevated liver enzymes occurred in 0.9 percent of patients (see WARNINGS).

Post Marketing Experience

There has been a single postmarketing report of paralysis (tetraparesis) associated with the combined use of verapamil and colchicine. This may have been caused by colchicine crossing the blood-brain barrier due to CYP3A4 and P-gp inhibition by verapamil. Combined use of verapamil and colchicine is not recommended (see PRECAUTIONS-Drug Interactions).

OVERDOSAGE

No specific information is available on the treatment of overdosage with TARKA.

Verapamil Component

Overdose with verapamil may lead to pronounced hypotension, bradycardia, and conduction system abnormalities (e.g., junctional rhythm with AV dissociation and high degree AV block, including asystole). Other symptoms secondary to hypoperfusion (e.g., metabolic acidosis, hyperglycemia, hyperkalemia, renal dysfunction, and convulsions) may be evident.

Treat all verapamil overdoses as serious and maintain observation for at least 48 hours, preferably under continuous hospital care. Delayed pharmacodynamic consequences may occur with the sustained release formulation. Verapamil is known to decrease gastrointestinal transit time. In cases of overdose, tablets of ISOPTIN SR have occasionally been reported to form concretions within the stomach or intestines. These concretions have not been visible on plain radiographs of the abdomen, and no medical means of gastrointestinal emptying is of proven efficacy in removing them. Endoscopy might reasonably be considered in cases of overdose when symptoms are unusually prolonged. Verapamil cannot be removed by hemodialysis.

Treatment of overdosage should be supportive. Beta adrenergic stimulation or parenteral administration of calcium solutions may increase calcium ion flux across the slow channel, and have been used effectively in treatment of deliberate overdosage with verapamil. The following measures may be considered:

Bradycardia and Conduction System Abnormalities

Atropine, isoproterenol, and cardiac pacing.

Hypotension

Intravenous fluids, vasopressors (e.g., dopamine, dobutamine), calcium solutions (e.g., 10% calcium chloride solution).

Cardiac Failures

Inotropic agents (e.g., isoproterenol, dopamine, dobutamine), diuretics. Asystole should be handled by the usual measures including cardiopulmonary resuscitation.

Trandolapril Component

The oral LD50 of trandolapril in mice was 4875 mg/kg in males and 3990 mg/kg in females. In rats, an oral dose of 5000 mg/kg caused low mortality (1 male out of 5; 0 females). In dogs, an oral dose of 1000 mg/kg did not cause mortality and abnormal clinical signs were not observed.

In humans, the most likely clinical manifestation would be symptoms attributable to severe hypotension. Laboratory determinations of serum levels of trandolapril and its metabolites are not widely available, and such determinations have, in any event, no established role in the management of trandolapril overdose. No data are available to suggest that physiological maneuvers (e.g., maneuvers to change pH of the urine) might accelerate elimination of trandolapril and its metabolites. It is not known if trandolapril or trandolaprilat can be usefully removed from the body by hemodialysis.

Angiotensin II could presumably serve as a specific antagonist antidote in the setting of trandolapril overdose, but angiotensin II is essentially unavailable outside of scattered research facilities. Because the hypotensive effect of trandolapril is achieved through vasodilation and effective hypovolemia, it is reasonable to treat trandolapril overdose by infusion of normal saline solution.

DOSAGE AND ADMINISTRATION

The recommended usual dosage range of trandolapril for hypertension is 1 to 4 mg per day administered in a single dose or two divided doses. The recommended usual dosage range of Isoptin-SR for hypertension is 120 to 480 mg per day administered in a single dose or two divided doses.

The hazards (see WARNINGS) of trandolapril are generally independent of dose; those of verapamil are a mixture of dose-dependent phenomena (primarily dizziness, AV block, constipation) and dose-independent phenomena, the former much more common than the latter. Therapy with any combination of trandolapril and verapamil will thus be associated with both sets of dose-independent hazards. The dose-dependent side effects of verapamil have not been shown to be decreased by the addition of trandolapril nor vice versa.

Rarely, the dose-independent hazards of trandolapril are serious. To minimize dose-independent hazards, it is usually appropriate to begin therapy with TARKA only after a patient has either (a) failed to achieve the desired antihypertensive effect with one or the other monotherapy at its respective maximally recommended dose and shortest dosing interval, or (b) the dose of one or the other monotherapy cannot be increased further because of dose-limiting side effects.

Clinical trials with TARKA have explored only once-a-day doses. The antihypertensive effect and or adverse effects of adding 4 mg of trandolapril once-a-day to a dose of 240 mg Isoptin-SR administered twice-a-day has not been studied, nor have the effects of adding as little of 180 mg Isoptin-SR to 2 mg trandolapril administered twice-a-day been evaluated. Over the dose range of Isoptin-SR 120 to 240 mg once-a-day and trandolapril 0.5 to 8 mg once-a-day, the effects of the combination increase with increasing doses of either component.

Replacement Therapy

For convenience, patients receiving trandolapril (up to 8 mg) and verapamil (up to 240 mg) in separate tablets, administered once-a-day, may instead wish to receive tablets of TARKA containing the same component doses.

TARKA should be administered with food.

HOW SUPPLIED

TARKA 2/180 mg tablets are supplied as pink, oval, film-coated tablets containing 2 mg trandolapril in an immediate release form and 180 mg verapamil hydrochloride in a sustained release form. The tablet is debossed with a triangle and 182 on one side and plain on the other side.

Bottles of 30 | NDC 54868-5548-2

TARKA 2/240 mg tablets are supplied as gold, oval, film-coated tablets containing 2 mg trandolapril in an immediate release form and 240 mg verapamil hydrochloride in a sustained release form. The tablet is debossed with a triangle and 242 on one side and plain on the other side.

Bottles of 10 | NDC 54868-5311-1
Bottles of 30 | NDC 54868-5311-0

TARKA 4/240 mg tablets are supplied as reddish-brown, oval, film-coated tablets containing 4 mg trandolapril in an immediate release form and 240 mg verapamil hydrochloride in a sustained release form. The tablet is debossed with a triangle and 244 on one side and plain on the other side.

Bottles of 10 | NDC 54868-5320-4
Bottles of 20 | NDC 54868-5320-1
Bottles of 30 | NDC 54868-5320-3
Bottles of 60 | NDC 54868-5320-0

Dispense in well-closed container with safety closure.

Storage

Store at 15°-25°C (59°-77°F) see USP.

Abbott Laboratories

North Chicago, IL 60064, U.S.A.

Rev: 1/2012 Abbott Laboratories

Relabeling and Repackaging by:
Physicians Total Care, Inc.
Tulsa, Oklahoma 74146

PACKAGE LABEL

Tarka®

Trandolapril/Verapamil

HCL ER

2 mg/180 mg

Rx only

Tarka®

Trandolapril/Verapamil

HCL ER

2 mg/240 mg

Rx only

Tarka®

Trandolapril/Verapamil

HCL ER

4 mg/240 mg

Rx only